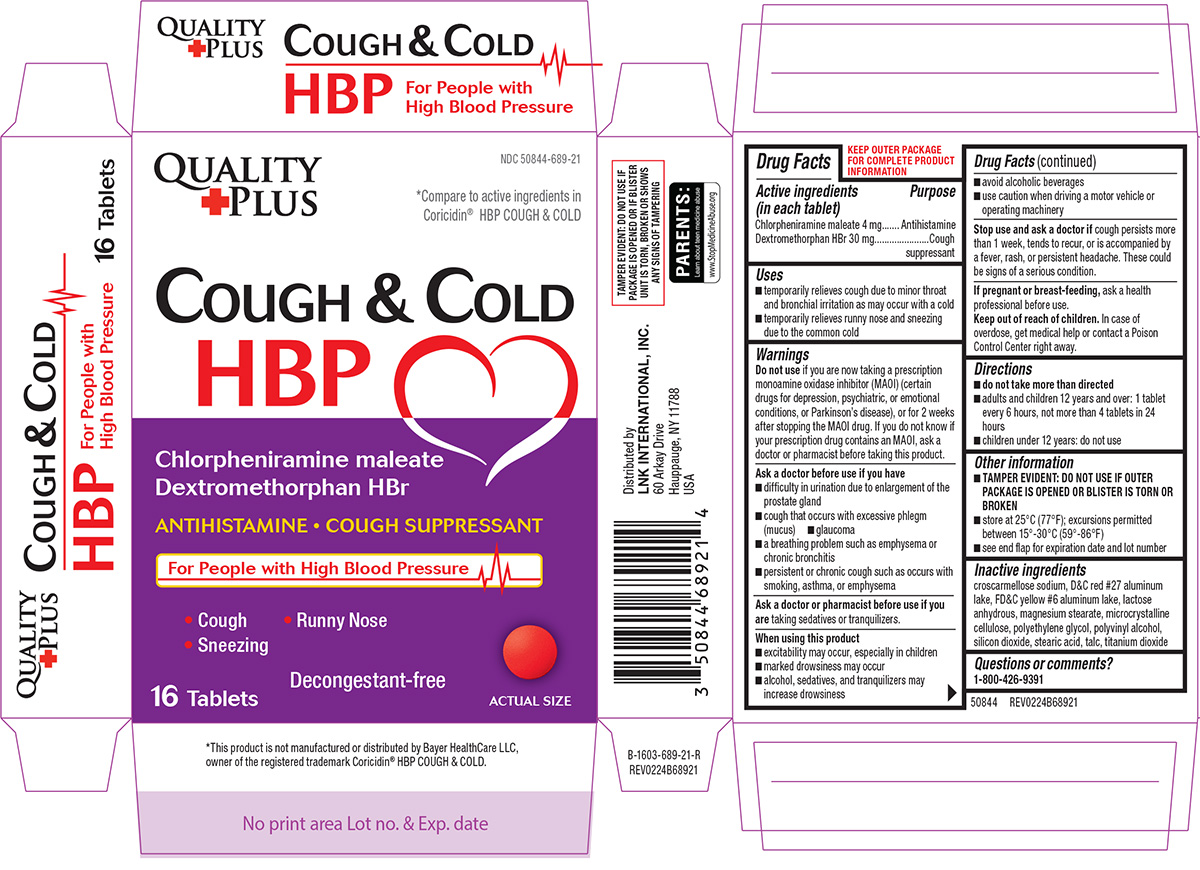 DRUG LABEL: Cough and Cold  HBP
NDC: 50844-689 | Form: TABLET, FILM COATED
Manufacturer: L.N.K. International, Inc.
Category: otc | Type: HUMAN OTC DRUG LABEL
Date: 20251203

ACTIVE INGREDIENTS: CHLORPHENIRAMINE MALEATE 4 mg/1 1; DEXTROMETHORPHAN HYDROBROMIDE 30 mg/1 1
INACTIVE INGREDIENTS: CROSCARMELLOSE SODIUM; D&C RED NO. 27 ALUMINUM LAKE; FD&C YELLOW NO. 6 ALUMINUM LAKE; ANHYDROUS LACTOSE; MAGNESIUM STEARATE; MICROCRYSTALLINE CELLULOSE; POLYETHYLENE GLYCOL, UNSPECIFIED; POLYVINYL ALCOHOL, UNSPECIFIED; SILICON DIOXIDE; STEARIC ACID; TALC; TITANIUM DIOXIDE

Quality Plus 44-689

Active ingredients (in each tablet)

Chlorpheniramine maleate 4 mg
Dextromethorphan HBr 30 mg

Purpose

Antihistamine
Cough suppressant

Uses

- temporarily relieves cough due to minor throat and bronchial irritation as may occur with a cold
- temporarily relieves runny nose and sneezing due to the common cold

Warnings

Do not use

if you are now taking a prescription monoamine oxidase inhibitor (MAOI) (certain drugs for depression, psychiatric, or emotional conditions, or Parkinson's disease), or for 2 weeks after stopping the MAOI drug. If you do not know if your prescription drug contains an MAOI, ask a doctor or pharmacist before taking this product.

Ask a doctor before use if you have

- difficulty in urination due to enlargement of the prostate gland
- cough that occurs with excessive phlegm (mucus)
- glaucoma
- a breathing problem such as emphysema or chronic bronchitis
- persistent or chronic cough such as occurs with smoking, asthma, or emphysema

Ask a doctor or pharmacist before use if you are

taking sedatives or tranquilizers.

When using this product

- excitability may occur, especially in children
- marked drowsiness may occur
- alcohol, sedatives, and tranquilizers may increase drowsiness
- avoid alcoholic beverages
- use caution when driving a motor vehicle or operating machinery

Stop use and ask a doctor if

cough persists more than 1 week, tends to recur, or is accompanied by a fever, rash, or persistent headache. These could be signs of a serious condition.

If pregnant or breast-feeding,

ask a health professional before use.

Keep out of reach of children.

In case of overdose, get medical help or contact a Poison Control Center right away.

Directions

- do not take more than directed
- adults and children 12 years and over: 1 tablet every 6 hours, not more than 4 tablets in 24 hours
- children under 12 years: do not use

Other information

- TAMPER EVIDENT: DO NOT USE IF OUTER PACKAGE IS OPENED OR BLISTER IS TORN OR BROKEN
- store at 25ºC (77ºF); excursions permitted between 15º-30ºC (59º-86ºF)
- see end flap for expiration date and lot number

Inactive ingredients

croscarmellose sodium, D&C red #27 aluminum lake, FD&C yellow #6 aluminum lake, lactose anhydrous, magnesium stearate, microcrystalline cellulose, polyethylene glycol, polyvinyl alcohol, silicon dioxide, stearic acid, talc, titanium dioxide

Questions or comments?

1-800-426-9391

Principal display panel

Quality
+Plus

NDC 50844-689-21

*Compare to active ingredients in Coricidin® HBP COUGH & COLD

COUGH & COLD HBP

Chlorpheniramine maleate
Dextromethorphan HBr

ANTIHISTAMINE • COUGH SUPPRESSANT

For People with High Blood Pressure

• Cough
• Sneezing
• Runny Nose

Decongestant-free

16 Tablets

ACTUAL SIZE

TAMPER EVIDENT: DO NOT USE IF PACKAGE IS OPENED OR IF BLISTER UNIT IS TORN, BROKEN OR SHOWS ANY SIGNS OF TAMPERING

*This product is not manufactured or distributed by Bayer HealthCare LLC, owner of the registered trademark Coricidin® HBP COUGH & COLD.

50844 REV0224B68921

Distributed by
LNK INTERNATIONAL, INC.
60 Arkay Drive
Hauppauge, NY 11788
USA

Quality plus 44-689